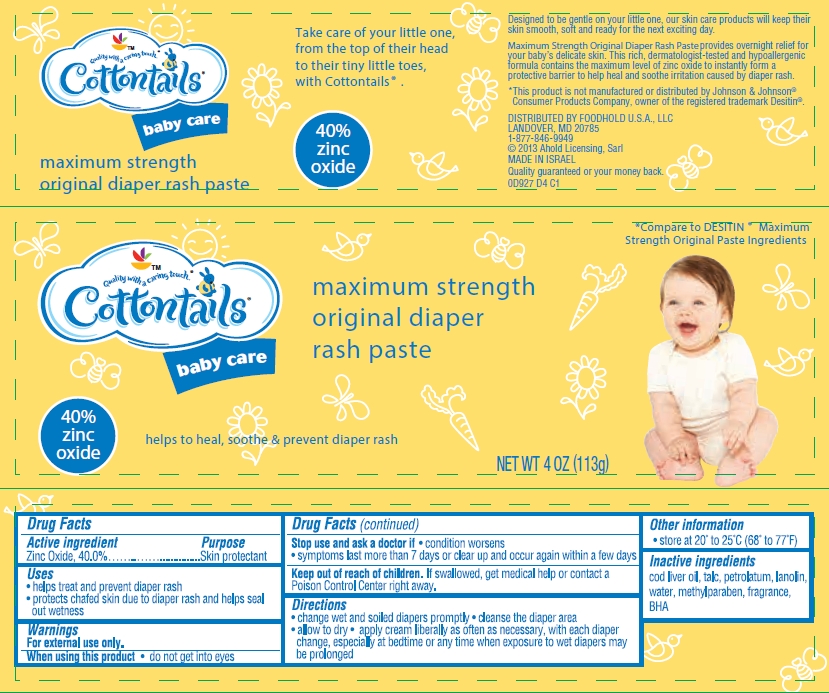 DRUG LABEL: Maximum Strength Original Diaper Rash
NDC: 41520-927 | Form: CREAM
Manufacturer: American Sales Company
Category: otc | Type: HUMAN OTC DRUG LABEL
Date: 20130930

ACTIVE INGREDIENTS: ZINC OXIDE 400 mg/1 g
INACTIVE INGREDIENTS: COD LIVER OIL; TALC; PETROLATUM; LANOLIN; WATER; METHYLPARABEN; BUTYLATED HYDROXYANISOLE

Cottontails Maximum Strength Original Diaper Rash Paste

Active ingredient

Zinc Oxide........40.0%

Purpose

Skin Protectant

Uses

- helps treat and prevent diaper rash
- protects chafed skin due to diaper rash and helps seal out wetness

Warnings

For external use only.

When using this product

- do not get into eyes

Stop use and ask a doctor if

- condition worsens
- symptoms last more than 7 days or clear up and occur again within a few days

Keep Out of Reach of Children.

If swallowed, get medical help or contact a Poison Control Center right away.

Directions

- change wet and soiled diapers promptly
- cleanse the diaper area
- allow to dry
- apply cream liberally as often as necessary, with each diaper change, especially at bedtime or any time when exposure to wet diapers may be prolonged

Other Information

- store at 20º to 25ºC (68º to 77ºF)

Inactive ingredients

cod liver oil, talc, petrolatum, lanolin, water, methylparaben, fragrance, BHA

Package/Label Principal Display Panel

Cottontails baby care

maximum strength original diaper rash paste

Take care of your little one, from the top of their head to their tiny little toes, with Cottontails®.

40% zinc oxide

Helps to heal, soothe & prevent diaper rash

Compare to Desitin® Maximum Strength Original Paste ingredients

NET WT. 4 OZ. (113 g)

Designed to be gentle on your little one, our skin care products will keep their skin smooth, soft and ready for the next exciting day.

Maximum Strength Original Diaper Rash Paste provides overnight relief for your baby's delicate skin. This rich, dermatologist-tested and hypoallergenic formula contains the maximum level of zinc oxide to instantly form a protective barrier to help heal and soothe irritation caused by diaper rash.

*This product is not manufactured or distributed by Johnson & Johnson® Consumer Products Company, owner of the registered trademark Desitin®

DISTRIBUTED BY FOODHOLD U.S.A., LLC
LANDOVER, MD 20785
1-877-846-9949
© 2013 Ahold Licensing, Sarl
MADE IN ISRAEL
Quality guaranteed or your money back.
0D927 D4 C1

Carton Label